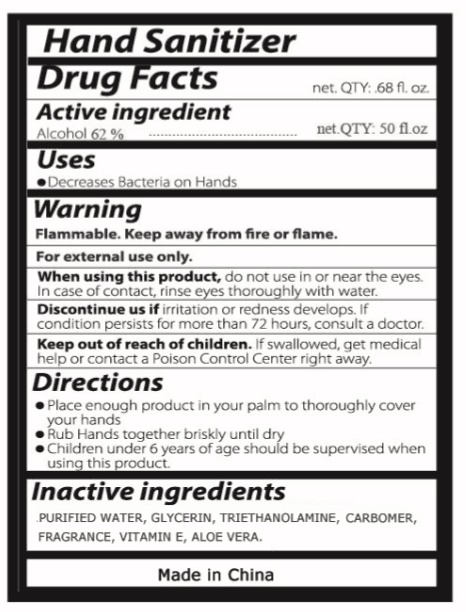 DRUG LABEL: HAND SANITIZER
NDC: 70675-958 | Form: LIQUID
Manufacturer: Deqing Jiarou Daily Chemical Co., Ltd
Category: otc | Type: HUMAN OTC DRUG LABEL
Date: 20200507

ACTIVE INGREDIENTS: ALCOHOL 62 mL/100 mL
INACTIVE INGREDIENTS: WATER; GLYCERIN; TROLAMINE; CARBOXYPOLYMETHYLENE; .ALPHA.-TOCOPHEROL; ALOE VERA LEAF

Hand Sanitizer

Active ingredient

Alcohol 62 %

Purpose

Antiseptic

Keep out of reach of children. If swallowed, get medical help or contact a Poison Control Center right away.

Uses

• Decreases Bacteria on Hands

Warning

Flammable. Keep away from fire or flame

For external use only.

When using this product, do not use in or near the eyes. In case of contact, rinse eyes thoroughly with water.

Discontinue use if irritation or redness develops. If condition persists for more than 72 hours, consult a doctor.

Directions

• Place enough product in your palm to thoroughly cover your hands

• Rub Hands together briskly until dry

• Children under 6 years of age should be supervised when using this product.

Inactive ingredients

PURIFIED WATER, GLYCERIN, TRIETHANOLAMINE, CARBOMER, FRAGRANCE, VITAMIN E, ALOE VERA.

Made in China